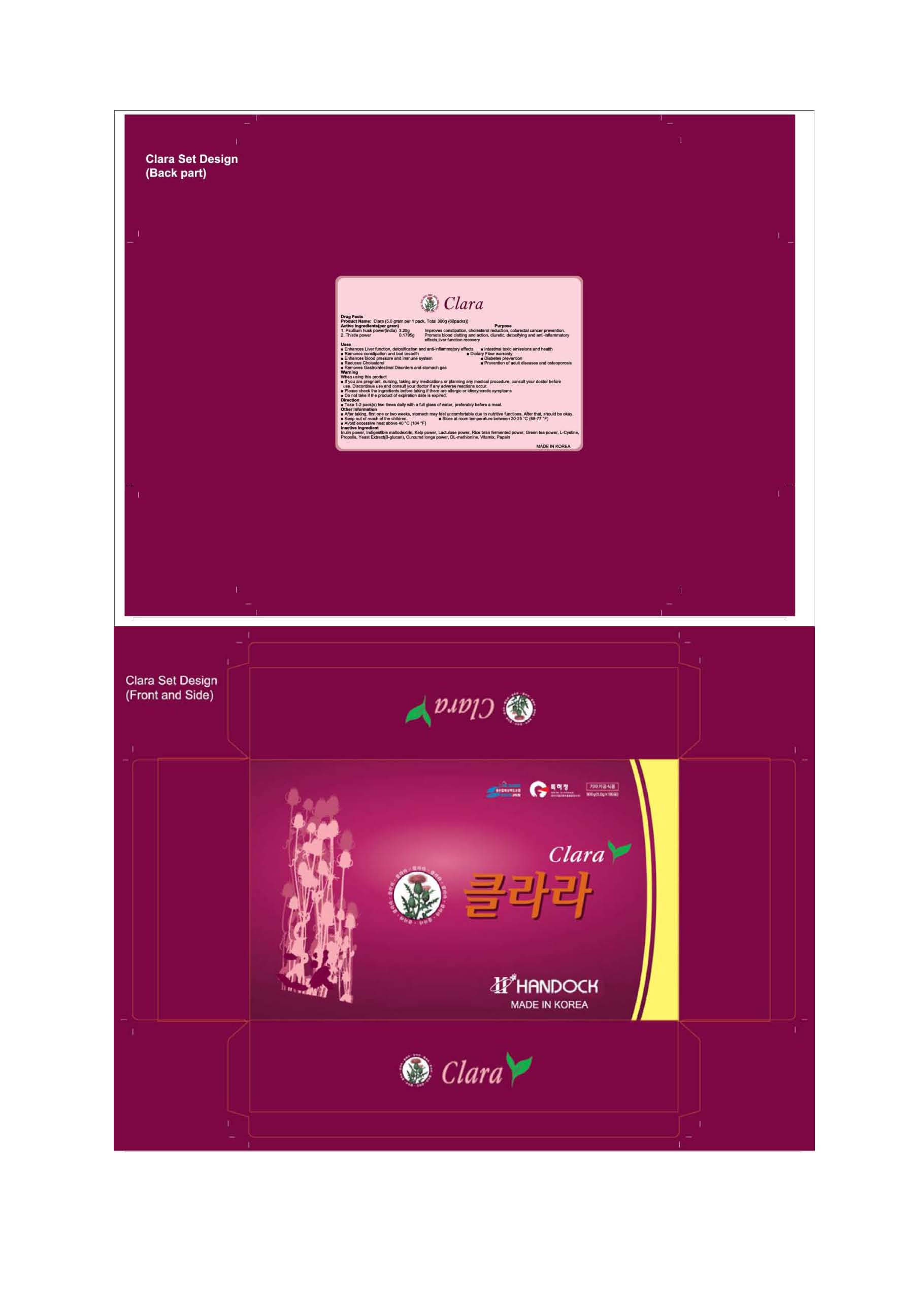 DRUG LABEL: Clara
NDC: 76369-1001 | Form: GRANULE
Manufacturer: Handock Cosmetics Inc
Category: otc | Type: HUMAN OTC DRUG LABEL
Date: 20110826

ACTIVE INGREDIENTS: PSYLLIUM HUSK 3.25 g/5 g
INACTIVE INGREDIENTS: INULIN; MALTODEXTRIN; KELP BASS; lactulose; RICE; TEA LEAF; CYSTINE; PROPOLIS WAX

Drug Facts

active ingredient: psyllium husk powder, thistle

inactive ingredient: Inulin power, Indigestible maltodextrin, Kelp power, Lactulose power, Rice bran fermented power, Green tea power, L-Cystine, Propolis, Yeast Extract(B-glucan), Curcumd longa power, DL-methionine, Vitamix, Papain

PURPOSE

■ Enhances Liver function, detoxification and anti-inflammatory effects
■ Intestinal toxic emissions and health
■ Removes constipation and bad breadth
■ Dietary Fiber warranty
■ Enhances blood pressure and immune system
■ Diabetes prevention
■ Reduces Cholesterol
■ Prevention of adult diseases and osteoporosis
■ Removes Gastrointestinal Disorders and stomach gas

keep out of reach of the children

INDICATIONS AND USAGE

Take 1-2 pack(s) two times daily with a full glass of water, preferably before a meal

WARNINGS

■ If you are pregnant, nursing, taking any medications or planning any medical procedure, consult your doctor before
use. Discontinue use and consult your doctor if any adverse reactions occur.
■ Please check the ingredients before taking if there are allergic or idiosyncratic symptoms
■ Do not take if the product of expiration date is expired

DOSAGE AND ADMINISTRATION

■ After taking, first one or two weeks, stomach may feel uncomfortable due to nutritive functions. After that, should be oka